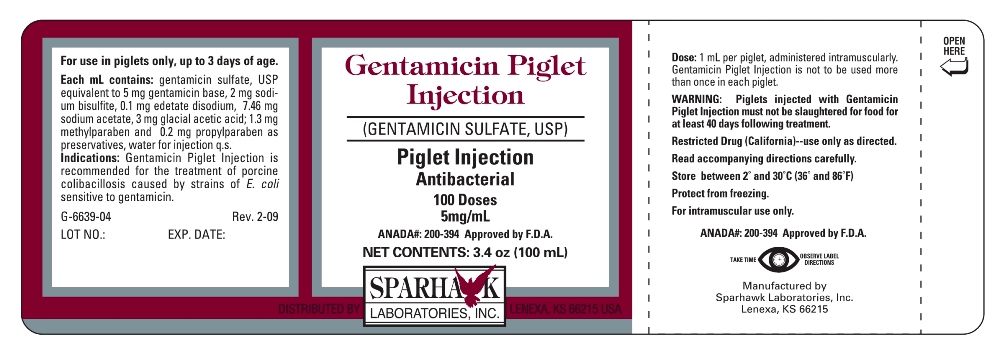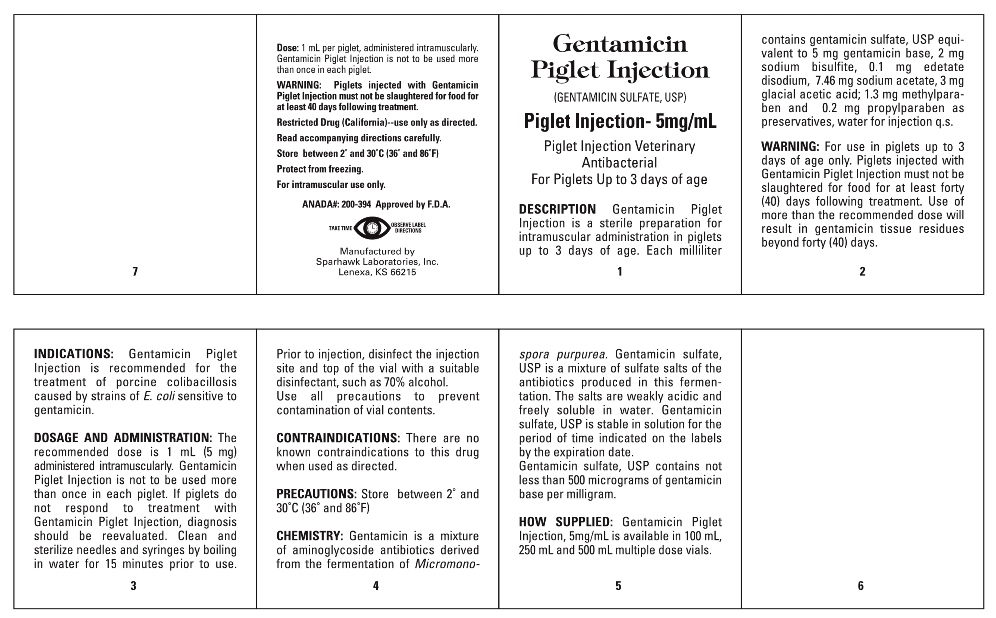 DRUG LABEL: GENTAMICIN PIGLET
NDC: 58005-663 | Form: INJECTION
Manufacturer: Sparhawk Laboratories, Inc.
Category: animal | Type: OTC ANIMAL DRUG LABEL
Date: 20130610

ACTIVE INGREDIENTS: GENTAMICIN SULFATE 5 mg/1 mL

Gentamicin Piglet Injection (GENTAMICIN SULFATE, USP) Piglet Injection - 5 mg/mL

Piglet Injection Veterinary

Antibacterial

For Piglets Up to 3 days of age

For intramuscular use only.

ANADA#: 200-394 Approved by F.D.A

DESCRIPTION

Gentamicin Piglet Injection is a sterile preparation for intramuscular administration in piglets up to 3 days of age. Each milliliter contains gentamicin sulfate, USP equivalent to 5 mg gentamicin base, 2 mg sodium bisulfite, 0.1 mg edetate disodium, 7.46 mg sodium acetate, 3 mg glacial acetic acid; 1.3 mg methylparaben and 0.2 mg propylparaben as preservatives, water for injection q.s.

WARNING

For use in piglets up to 3 days of age only.

Piglets injected with Gentamicin Piglet Injection must not be slaughtered for food for at least forty (40) days following treatment. Use of more than the recommended dose will result in gentamicin tissue residues beyond forty (40) days.

Restricted Drug (California)--use only as directed.

Read accompanying directions carefully.

INDICATIONS

Gentamicin Piglet Injection is recommended for the treatment of porcine colibacillosis caused by strains of E. coli sensitive to gentamicin.

DOSAGE AND ADMINISTRATION

The recommended dose is 1 mL (5 mg) administered intramuscularly. Gentamicin Piglet Injection is not to be used more than once in each piglet. If piglets do not respond to treatment with Gentamicin Piglet Injection, diagnosis should be reevaluated. Clean and sterilize needles and syringes by boiling in water for 15 minutes prior to use. Prior to injection, disinfect the injection site and top the vial with a suitable disinfectant, such as 70% alcohol. Use all precautions to prevent contamination of vial contents.

CONTRAINDICATIONS

There are no known contraindications to this drug when used as directed.

PRECAUTIONS

Store between 2o and 30oC (36o and 86oF)

CHEMISTRY

Gentamicin is a mixture of aminoglycoside antibiotics derived from the fermentation of Micromonospora purpurea. Gentamicin Sulfate, USP is a mixture of sulfate salts of the antibiotics produced in the fermentation. The salts are weakly acidic and freely soluble in water. Gentamicin sulfate, USP is stable in solution for the period of time indicated on the labels by the expiration date.

Gentamicin sulfate, USP contains not less than 500 micrograms of gentamicin base per milligram.

HOW SUPPLIED

Enter section text here

STORAGE AND HANDLING

Store between 2o and 30oC (36oand 86oF)

Protect from freezing.

For intramuscular use only.

TAKE TIME OBSERVE LABEL DIRECTIONS

PACKAGE LABEL

Manufactured by
Sparhawk Laboratories, Inc.
Lenexa, KS 66215

G-6639-04 Rev. 2-09